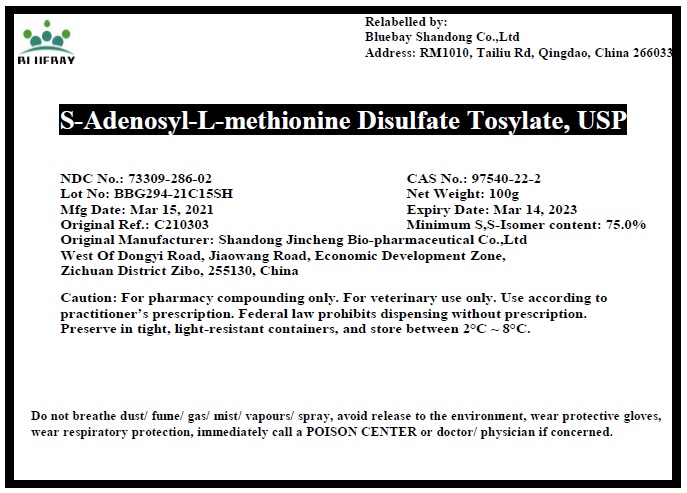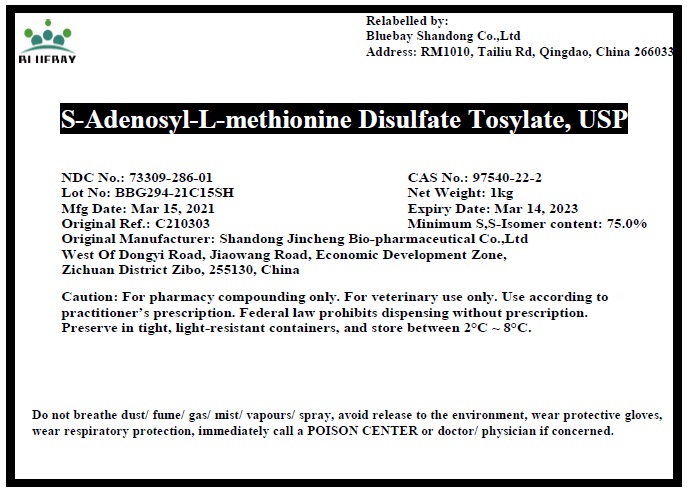 DRUG LABEL: S-Adenosyl-L-methionine Disulfate Tosylate
NDC: 73309-286 | Form: POWDER
Manufacturer: BLUEBAY SHANDONG CO.,LTD
Category: other | Type: BULK INGREDIENT
Date: 20210602

ACTIVE INGREDIENTS: S-ADENOSYL-L-METHIONINE DISULFATE TOSYLATE 1 g/1 g

S-Adenosyl-L-methionine Disulfate Tosylate